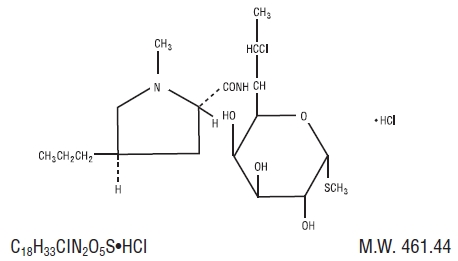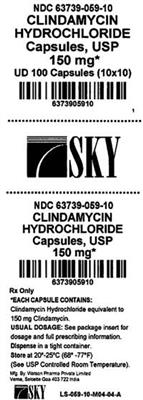 DRUG LABEL: Clindamycin Hydrochloride
NDC: 63739-059 | Form: CAPSULE
Manufacturer: McKesson Corporation dba Sky Packaging
Category: prescription | Type: HUMAN PRESCRIPTION DRUG LABEL
Date: 20210120

ACTIVE INGREDIENTS: CLINDAMYCIN HYDROCHLORIDE 150 mg/1 1
INACTIVE INGREDIENTS: ANHYDROUS LACTOSE; MAGNESIUM STEARATE; STARCH, CORN; TALC; D&C RED NO. 28; FD&C BLUE NO. 1; FD&C RED NO. 40; GELATIN, UNSPECIFIED; SILICON DIOXIDE; SODIUM LAURYL SULFATE; TITANIUM DIOXIDE; FERROSOFERRIC OXIDE; FERRIC OXIDE YELLOW

Clindamycin
Hydrochloride
Capsules USP

Rx only
Revised: March 2009

To reduce the development of drug-resistant bacteria and maintain the effectiveness of clindamycin HCl and other antibacterial drugs, clindamycin hydrochloride should be used only to treat or prevent infections that are proven or strongly suspected to be caused by bacteria.

WARNING

Pseudomembranous colitis has been reported with nearly all antibacterial agents, including clindamycin, and may range in severity from mild to life-threatening. Therefore, it is important to consider this diagnosis in patients who present with diarrhea subsequent to the administration of antibacterial agents.

Because clindamycin therapy has been associated with severe colitis which may end fatally, it should be reserved for serious infections where less toxic antimicrobial agents are inappropriate, as described in the INDICATIONS AND USAGE section. It should not be used in patients with nonbacterial infections such as most upper respiratory tract infections. Treatment with antibacterial agents alters the normal flora of the colon and may permit overgrowth of clostridia. Studies indicate that a toxin produced by Clostridium difficile is one primary cause of “antibiotic-associated colitis”.

After the diagnosis of pseudomembranous colitis has been established, therapeutic measures should be initiated. Mild cases of pseudomembranous colitis usually respond to drug discontinuation alone. In moderate to severe cases, consideration should be given to management with fluids and electrolytes, protein supplementation, and treatment with an antibacterial drug clinically effective against C. difficile colitis.

Diarrhea, colitis, and pseudomembranous colitis have been observed to begin up to several weeks following cessation of therapy with clindamycin.

DESCRIPTION

Clindamycin hydrochloride is the hydrated hydrochloride salt of clindamycin. Clindamycin is a semisynthetic antibiotic produced by a 7(S)-chloro-substitution of the 7(R)-hydroxyl group of the parent compound lincomycin.

The chemical name for clindamycin hydrochloride is Methyl 7-chloro-6,7,8-trideoxy-6-(1-methyl- trans-4-propyl-L-2-pyrrolidinecarboxamido)-1-thio-L- threo-α-D- galacto-octopyranoside monohydrochloride. The structural formula is represented below:

Clindamycin Hydrochloride Capsules USP (equivalent to 150 mg or 300 mg clindamycin) contain the following inactive ingredients: anhydrous lactose, magnesium stearate, starch (corn) and talc. The capsule shells contain: D&C Red No. 28, FD&C Blue No. 1, FD&C Red No. 40, gelatin, silicon dioxide, sodium lauryl sulfate, and titanium dioxide. The 150 mg capsule shell also contains black iron oxide and yellow iron oxide.

CLINICAL PHARMACOLOGY

Human Pharmacology: Serum level studies with a 150 mg oral dose of clindamycin hydrochloride in 24 normal adult volunteers showed that clindamycin was rapidly absorbed after oral administration. An average peak serum level of 2.50 mcg/mL was reached in 45 minutes; serum levels averaged 1.51 mcg/mL at 3 hours and 0.70 mcg/mL at 6 hours. Absorption of an oral dose is virtually complete (90%), and the concomitant administration of food does not appreciably modify the serum concentrations; serum levels have been uniform and predictable from person to person and dose to dose. Serum level studies following multiple doses of clindamycin hydrochloride for up to 14 days show no evidence of accumulation or altered metabolism of drug.

Serum half-life of clindamycin is increased slightly in patients with markedly reduced renal function. Hemodialysis and peritoneal dialysis are not effective in removing clindamycin from the serum.

Concentrations of clindamycin in the serum increased linearly with increased dose. Serum levels exceed the MIC (minimum inhibitory concentration) for most indicated organisms for at least six hours following administration of the usually recommended doses. Clindamycin is widely distributed in body fluids and tissues (including bones). The average biological half-life is 2.4 hours. Approximately 10% of the bioactivity is excreted in the urine and 3.6% in the feces; the remainder is excreted as bioinactive metabolites.

Doses of up to 2 grams of clindamycin per day for 14 days have been well tolerated by healthy volunteers, except that the incidence of gastrointestinal side effects is greater with the higher doses.

No significant levels of clindamycin are attained in the cerebrospinal fluid, even in the presence of inflamed meninges.

Pharmacokinetic studies in elderly volunteers (61-79 years) and younger adults (18-39 years) indicate that age alone does not alter clindamycin pharmacokinetics (clearance, elimination half-life, volume of distribution, and area under the serum concentration-time curve) after IV administration of clindamycin phosphate. After oral administration of clindamycin hydrochloride, elimination half-life is increased to approximately 4.0 hours (range 3.4-5.1 h) in the elderly compared to 3.2 hours (range 2.1-4.2 h) in younger adults. The extent of absorption, however, is not different between age groups and no dosage alteration is necessary for the elderly with normal hepatic function and normal (age-adjusted) renal function.

Microbiology: Clindamycin inhibits bacterial protein synthesis by binding to the 50S subunit of the ribosome. It has activity against Gram-positive aerobes and anaerobes as well as the Gram-negative anaerobes. Clindamycin is bacteriostatic. Cross-resistance between clindamycin and lincomycin is complete. Antagonism in vitro has been demonstrated between clindamycin and erythromycin.

Clindamycin has been shown to be active against most of the isolates of the following microorganisms, both in vitro and in clinical infections, as described in the INDICATIONS AND USAGE section.

Gram-positive aerobes

Staphylococcus aureus (methicillin-susceptible strains)

Streptococcus pneumoniae (penicillin-susceptible strains)

Streptococcus pyogenes

Anaerobes

Prevotella melaninogenica

Fusobacterium necrophorum

Fusobacterium nucleatum

Peptostreptococcus anaerobius

Clostridium perfringens

The following in vitro data are available, but their clinical significance is unknown. At least 90% of the following microorganisms exhibit an in vitro minimum inhibitory concentration (MIC) less than or equal to the susceptible breakpoint for clindamycin. However, the safety and effectiveness of clindamycin in treating clinical infections due to these microorganisms have not been established in adequate and well-controlled clinical trials.

Gram-positive aerobes

Staphylococcus epidermidis (methicillin-susceptible strains)

Streptococcus agalactiae

Streptococcus anginosus

Streptococcus oralis

Streptococcus mitis

Anaerobes

Prevotella intermedia

Prevotella bivia

Propionibacterium acnes

Micromonas (“Peptostreptococcus”) micros

Finegoldia (“Peptostreptococcus”) magna

Actinomyces israelii

Clostridium clostridioforme

Eubacterium lentum

SUSCEPTIBILITY TESTING METHODS

NOTE: Susceptibility testing by dilution methods requires the use of clindamycin susceptibility powder.

When available, the results of in vitro susceptibility tests should be provided to the physician as periodic reports that describe the susceptibility profile of nosocomial and community-acquired pathogens. These reports should aid the physician in selecting the most effective antimicrobial.

Dilution Techniques: Quantitative methods are used to determine antimicrobial minimum inhibitory concentrations (MICs). These MICs provide estimates of the susceptibility of bacteria to antimicrobial compounds. The MICs should be determined using a standardized procedure. Standardized procedures are based on a dilution method (broth and agar)^1,2,3 or equivalent with standardized inoculum concentrations and standardized concentrations of clindamycin powder. The MIC values should be interpreted according to the criteria provided in Table 1.

Diffusion Techniques: Quantitative methods that require the measurement of zone diameters also provide reproducible estimates of the susceptibility of bacteria to antimicrobial compounds. One such standardized procedure^2,3 requires the use of standardized inoculum concentrations. This procedure uses paper disks impregnated with 2 mcg of clindamycin to test the susceptibility of microorganisms to clindamycin. The disk diffusion interpretive criteria are provided in Table 1.

Table 1. Susceptibility Interpretive Criteria for Clindamycin
 | Susceptibility Interpretive Criteria
 | Minimal Inhibitory
 | Concentrations |  |  | Disk Diffusion
Pathogen | (MIC in mcg/mL) |  |  | (Zone Diameters in mm)
 | S | I | R | S | I | R
Staphylococcus spp. | ≤0.5 | 1-2 | ≥4 | ≥21 | 15-20 | ≤14
Streptococcus
pneumoniae and other | ≤0.25a | 0.5 | ≥1 | ≥19b | 16-18 | ≤15
Streptococcus spp.
Anaerobic Bacteriac | ≤2 | 4 | ≥8 | NA | NA | NA
a These interpretive standards for S. pneumoniae and other Streptococcus spp. are applicable only to tests performed by broth microdilution using cation-adjusted Mueller-Hinton broth with 2 to 5% lysed horse blood inoculated with a direct colony suspension and incubated in ambient air at 35°C for 20 to 24 hours.
b These zone diameter interpretive standards are applicable only to tests performed using Mueller-Hinton agar supplemented with 5% sheep blood inoculated with a direct colony suspension and incubated in 5% CO2 at 35°C for 20 to 24 hours.
c These interpretive criteria are for all anaerobic bacterial pathogens; no organism specific interpretive criteria are available.
NA=not applicable

A report of “Susceptible” indicates that the pathogen is likely to be inhibited if the antimicrobial compound in the blood reaches the concentrations usually achievable. A report of “Intermediate” indicates that the result should be considered equivocal, and, if the microorganism is not fully susceptible to alternative, clinically feasible drugs, the test should be repeated. This category implies possible clinical applicability in body sites where the drug is physiologically concentrated or in situations where high dosage of drug can be used. This category also provides a buffer zone that prevents small, uncontrolled technical factors from causing major discrepancies in interpretation. A report of “Resistant” indicates that the pathogen is not likely to be inhibited if the antimicrobial compound in the blood reaches the concentrations usually achievable; other therapy should be selected.

Quality Control

Standardized susceptibility test procedures require the use of quality control microorganisms to control the technical aspects of the test procedures. Standard clindamycin powder should provide the following range of values noted in Table 2. NOTE: Quality control microorganisms are specific strains of organisms with intrinsic biological properties relating to resistance mechanisms and their genetic expression within bacteria; the specific strains used for microbiological quality control are not clinically significant.

Table 2. Acceptable Quality Control Ranges for Clindamycin to be Used in Validation of Susceptibility Test Results
 | Acceptable Quality Control Ranges
 | Minimum Inhibitory
 | Concentrations | Disk Diffusion
QC Strain | (MIC in mcg/mL) | (Zone Diameters in mm)
When Testing
Aerobic Pathogens
Staphylococcus aureus | 0.06–0.25 | NA
ATCC 29213
Staphylococcus aureus | NA | 24–30
ATCC 25923
Streptococcus | 0.03–0.12e | 19–25f
pneumoniae
ATCC 49619d
When Testing
Strict Anaerobes
Bacteroides fragilis | 0.5–2 | NA
ATCC 25285
Bacteroides | 2–8 | NA
thetaiotaomicron
ATCC 29741
Eubacterium lentum | 0.06–0.25 | NA
ATCC 43055
NA=Not applicable
d This organism may be used for validation of susceptibility test results when testing Streptococcus spp. other than S. pneumoniae.
e This quality control range for S. pneumoniae is applicable only to tests performed by broth microdilution using cation-adjusted Mueller-Hinton broth with 2 to 5% lysed horse blood inoculated with a direct colony suspension and incubated in ambient air at 35°C for 20 to 24 hours.
f This quality control zone diameter range is applicable only to tests performed using Mueller-Hinton agar supplemented with 5% sheep blood inoculated with a direct colony suspension and incubated in 5% CO2 at 35°C for 20 to 24 hours.
ATCC® is a registered trademark of the American Type Culture Collection

INDICATIONS AND USAGE

Clindamycin is indicated in the treatment of serious infections caused by susceptible anaerobic bacteria.

Clindamycin is also indicated in the treatment of serious infections due to susceptible strains of streptococci, pneumococci, and staphylococci. Its use should be reserved for penicillin-allergic patients or other patients for whom, in the judgment of the physician, a penicillin is inappropriate. Because of the risk of colitis, as described in the WARNING box, before selecting clindamycin the physician should consider the nature of the infection and the suitability of less toxic alternatives (e.g., erythromycin).

Anaerobes: Serious respiratory tract infections such as empyema, anaerobic pneumonitis and lung abscess; serious skin and soft tissue infections; septicemia; intra-abdominal infections such as peritonitis and intra-abdominal abscess (typically resulting from anaerobic organisms resident in the normal gastrointestinal tract); infections of the female pelvis and genital tract such as endometritis, nongonococcal tubo-ovarian abscess, pelvic cellulitis and postsurgical vaginal cuff infection.

Streptococci: Serious respiratory tract infections; serious skin and soft tissue infections.

Staphylococci: Serious respiratory tract infections; serious skin and soft tissue infections.

Pneumococci: Serious respiratory tract infections.

Bacteriologic studies should be performed to determine the causative organisms and their susceptibility to clindamycin.

To reduce the development of drug-resistant bacteria and maintain the effectiveness of clindamycin hydrochloride and other antibacterial drugs, clindamycin hydrochloride should be used only to treat or prevent infections that are proven or strongly suspected to be caused by susceptible bacteria. When culture and susceptibility information are available, they should be considered in selecting or modifying antibacterial therapy. In the absence of such data, local epidemiology and susceptibility patterns may contribute to the empiric selection of therapy.

CONTRAINDICATIONS

Clindamycin hydrochloride capsules are contraindicated in individuals with a history of hypersensitivity to preparations containing clindamycin or lincomycin.

WARNINGS

See WARNING box.

Pseudomembranous colitis has been reported with nearly all antibacterial agents, including clindamycin, and may range in severity from mild to life-threatening. Therefore, it is important to consider this diagnosis in patients who present with diarrhea subsequent to the administration of antibacterial agents.

Treatment with antibacterial agents alters the normal flora of the colon and may permit overgrowth of clostridia. Studies indicate that a toxin produced by Clostridium difficile is one primary cause of “antibiotic-associated colitis.”

After the diagnosis of pseudomembranous colitis has been established, therapeutic measures should be initiated. Mild cases of pseudomembranous colitis usually respond to drug discontinuation alone. In moderate to severe cases, consideration should be given to management with fluids and electrolytes, protein supplementation, and treatment with an antibacterial drug clinically effective against C. difficile colitis.

A careful inquiry should be made concerning previous sensitivities to drugs and other allergens.

Usage in Meningitis–Since clindamycin does not diffuse adequately into the cerebrospinal fluid, the drug should not be used in the treatment of meningitis.

PRECAUTIONS

General

Review of experience to date suggests that a subgroup of older patients with associated severe illness may tolerate diarrhea less well. When clindamycin is indicated in these patients, they should be carefully monitored for change in bowel frequency.

Clindamycin hydrochloride should be prescribed with caution in individuals with a history of gastrointestinal disease, particularly colitis.

Clindamycin hydrochloride should be prescribed with caution in atopic individuals.

Indicated surgical procedures should be performed in conjunction with antibiotic therapy.

The use of clindamycin hydrochloride occasionally results in overgrowth of nonsusceptible organisms–particularly yeasts. Should superinfections occur, appropriate measures should be taken as indicated by the clinical situation.

Clindamycin dosage modification may not be necessary in patients with renal disease. In patients with moderate to severe liver disease, prolongation of clindamycin half-life has been found. However, it was postulated from studies that when given every eight hours, accumulation should rarely occur. Therefore, dosage modification in patients with liver disease may not be necessary. However, periodic liver enzyme determinations should be made when treating patients with severe liver disease.

Prescribing clindamycin hydrochloride in the absence of a proven or strongly suspected bacterial infection or a prophylactic indication is unlikely to provide benefit to the patient and increases the risk of the development of drug-resistant bacteria.

Information for Patients

Patients should be counseled that antibacterial drugs including clindamycin hydrochloride should only be used to treat bacterial infections. They do not treat viral infections (e.g., the common cold). When clindamycin hydrochloride is prescribed to treat a bacterial infection, patients should be told that although it is common to feel better early in the course of therapy, the medication should be taken exactly as directed. Skipping doses or not completing the full course of therapy may (1) decrease the effectiveness of the immediate treatment and (2) increase the likelihood that bacteria will develop resistance and will not be treatable by clindamycin hydrochloride or other antibacterial drugs in the future.

Laboratory Tests

During prolonged therapy, periodic liver and kidney function tests and blood counts should be performed.

Drug Interactions

Clindamycin has been shown to have neuromuscular blocking properties that may enhance the action of other neuromuscular blocking agents. Therefore, it should be used with caution in patients receiving such agents.

Antagonism has been demonstrated between clindamycin and erythromycin in vitro. Because of possible clinical significance, these two drugs should not be administered concurrently.

Carcinogenesis, Mutagenesis, Impairment of Fertility

Long term studies in animals have not been performed with clindamycin to evaluate carcinogenic potential. Genotoxicity tests performed included a rat micronucleus test and an Ames Salmonella reversion test. Both tests were negative.

Fertility studies in rats treated orally with up to 300 mg/kg/day (approximately 1.6 times the highest recommended adult human dose based on mg/m^2) revealed no effects on fertility or mating ability.

Pregnancy

Teratogenic effects

Pregnancy category B

Reproduction studies performed in rats and mice using oral doses of clindamycin up to 600 mg/kg/day (3.2 and 1.6 times the highest recommended adult human dose based on mg/m^2, respectively) or subcutaneous doses of clindamycin up to 250 mg/kg/day (1.3 and 0.7 times the highest recommended adult human dose based on mg/m^2, respectively) revealed no evidence of teratogenicity.

There are, however, no adequate and well-controlled studies in pregnant women. Because animal reproduction studies are not always predictive of the human response, this drug should be used during pregnancy only if clearly needed.

Nursing Mothers

Clindamycin has been reported to appear in breast milk in the range of 0.7 to 3.8 mcg/mL.

Pediatric Use

When clindamycin hydrochloride is administered to the pediatric population (birth to 16 years), appropriate monitoring of organ system functions is desirable.

Geriatric Use

Clinical studies of clindamycin did not include sufficient numbers of patients age 65 and over to determine whether they respond differently from younger patients. However, other reported clinical experience indicates that antibiotic-associated colitis and diarrhea (due to Clostridium difficile) seen in association with most antibiotics occur more frequently in the elderly (>60 years) and may be more severe. These patients should be carefully monitored for the development of diarrhea.

Pharmacokinetic studies with clindamycin have shown no clinically important differences between young and elderly subjects with normal hepatic function and normal (age-adjusted) renal function after oral or intravenous administration.

ADVERSE REACTIONS

The following reactions have been reported with the use of clindamycin.

Gastrointestinal

Abdominal pain, pseudomembranous colitis, esophagitis, nausea, vomiting and diarrhea (see WARNING box). The onset of pseudomembranous colitis symptoms may occur during or after antibacterial treatment (see WARNINGS).

Hypersensitivity Reactions

Generalized mild to moderate morbilliform-like (maculopapular) skin rashes are the most frequently reported adverse reactions. Vesiculobullous rashes, as well as urticaria, have been observed during drug therapy. Rare instances of erythema multiforme, some resembling Stevens-Johnson syndrome, and a few cases of anaphylactoid reactions have also been reported.

Skin and Mucous Membranes

Pruritus, vaginitis, and rare instances of exfoliative dermatitis have been reported. (See Hypersensitivity Reactions.)

Liver

Jaundice and abnormalities in liver function tests have been observed during clindamycin therapy.

Renal

Although no direct relationship of clindamycin to renal damage has been established, renal dysfunction as evidenced by azotemia, oliguria, and/or proteinuria has been observed in rare instances.

Hematopoietic

Transient neutropenia (leukopenia) and eosinophilia have been reported. Reports of agranulocytosis and thrombocytopenia have been made. No direct etiologic relationship to concurrent clindamycin therapy could be made in any of the foregoing.

Musculoskeletal

Rare instances of polyarthritis have been reported.

OVERDOSAGE

Significant mortality was observed in mice at an intravenous dose of 855 mg/kg and in rats at an oral or subcutaneous dose of approximately 2618 mg/kg. In the mice, convulsions and depression were observed.

Hemodialysis and peritoneal dialysis are not effective in removing clindamycin from the serum.

DOSAGE AND ADMINISTRATION

If significant diarrhea occurs during therapy, this antibiotic should be discontinued (see WARNING box).

Adults: Serious infections–150 to 300 mg every 6 hours. More severe infections–300 to 450 mg every 6 hours.

Pediatric Patients: Serious infections–8 to 16 mg/kg/day (4 to 8 mg/lb/day) divided into three or four equal doses. More severe infections–16 to 20 mg/kg/day (8 to 10 mg/lb/day) divided into three or four equal doses.

To avoid the possibility of esophageal irritation, clindamycin hydrochloride capsules should be taken with a full glass of water.

Serious infections due to anaerobic bacteria are usually treated with clindamycin phosphate injection. However, in clinically appropriate circumstances, the physician may elect to initiate treatment or continue treatment with clindamycin hydrochloride capsules.

In cases of β-hemolytic streptococcal infections, treatment should continue for at least 10 days.

HOW SUPPLIED

Product: 63739-059

NDC: 63739-059-10 100 CAPSULE in a BLISTER PACK

ANIMAL TOXICOLOGY

One year oral toxicity studies in Spartan Sprague-Dawley rats and beagle dogs at dose levels up to 300 mg/kg/day (approximately 1.6 and 5.4 times the highest recommended adult human dose based on mg/m^2, respectively) have shown clindamycin to be well tolerated. No appreciable difference in pathological findings has been observed between groups of animals treated with clindamycin and comparable control groups. Rats receiving clindamycin hydrochloride at 600 mg/kg/day (approximately 3.2 times the highest recommended adult human dose based on mg/m^2) for 6 months tolerated the drug well; however, dogs dosed at this level (approximately 10.8 times the highest recommended adult human dose based on mg/m^2) vomited, would not eat, and lost weight.

REFERENCES

1. NCCLS. Methods for Dilution Antimicrobial Susceptibility Tests for Bacteria that Grow Aerobically; Approved Standard-5th ed. NCCLS document M7-A5, 2000. NCCLS, 940 West Valley Road, Suite 1400, Wayne, PA 19087-1898.

2. NCCLS. Performance Standards for Antimicrobial Susceptibility Testing: 13th Informational Supplement. NCCLS document M100-S13 (M2 & M7), 2003. NCCLS, 940 West Valley Road, Suite 1400, Wayne, PA 19087-1898.

3. NCCLS. Methods for Antimicrobial Susceptibility Testing of Anaerobic Bacteria 5th ed. Approved Standard. NCCLS document M11-A5, 2001. NCCLS, 940 West Valley Road, Suite 1400, Wayne, PA 19087-1898.

4. NCCLS. Performance Standards for Antimicrobial Disk Susceptibility Tests; Approved Standard-8th ed. NCCLS document M2-A8 (ISBN 1-56238-393-0), 2003. NCCLS, 940 West Valley Road, Suite 1400, Wayne, PA 19087-1898.

Manufactured By:
Watson Pharma Private Limited
Verna, Salcette Goa 403 722 INDIA

Distributed By:
McKesson Packaging
Concord, NC 28027

Revised: March 2009

0309B

IS-059-M04-04-A